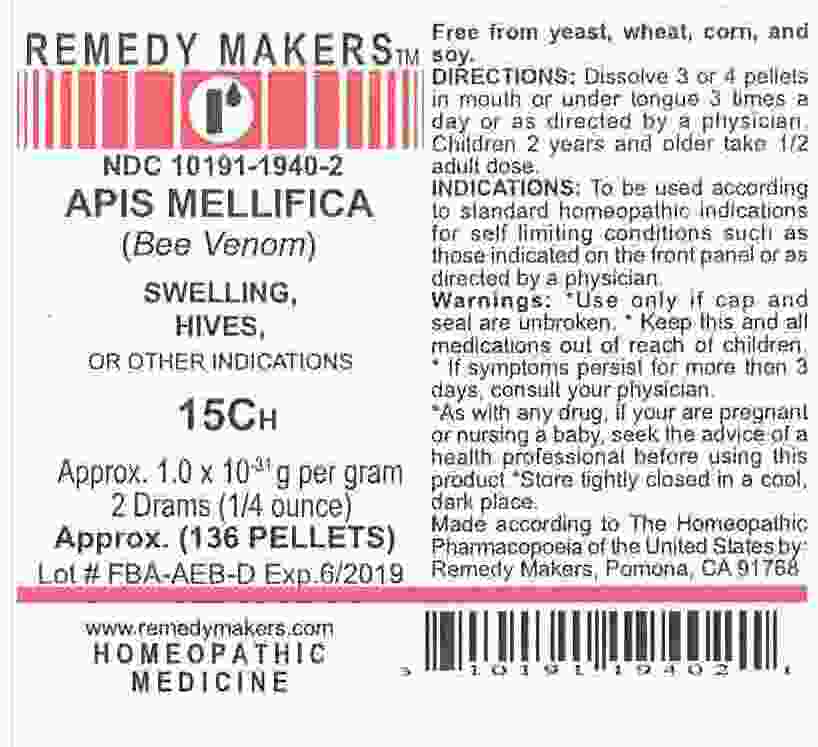 DRUG LABEL: APIS MELLIFICA
NDC: 10191-1940 | Form: PELLET
Manufacturer: Remedy Makers 
Category: homeopathic | Type: HUMAN OTC DRUG LABEL
Date: 20101018

ACTIVE INGREDIENTS: APIS MELLIFERA 15 [hp_C]/1 1
INACTIVE INGREDIENTS: SUCROSE; LACTOSE

APIS MELLIFICA 15C (Bee Venom)

ACTIVE INGREDIENT

APIS MELLIFERA

PURPOSE

SWELLING, HIVES , OR OTHER INDICATIONS

KEEP OUT OF REACH OF CHILDREN

WARNING: Keep this and all medications out of reach of children.

INDICATIONS AND USAGE

INDICATIONS: To be used according to standard homeopathic indications for self limiting conditions such as those indicated on the front panel or as directed by a physician.

Free from yeast, wheat, corn, and soy.

WARNINGS

WARNING SECTION: Use only if cap and seal are unbroken. If symptoms persist for more then 3 days, consult your physician. As with any drug, if your pregnant or nursing a baby, seek the advise of a health professional before using this product. Store tightly closed in a cool, dark place. Made according to The Homeopathic Pharmacopoeia of the United States by: Remedy Makers, Pomona, CA 91768

DOSAGE AND ADMINISTRATION

DIRECTIONS: Dissolve 3 or 4 in mouth or tongue 3 times a day or as directed by a physician. Children 2 years and older take 1/2 adult dose.

INACTIVE INGREDIENT

80% sucrose / 20% lactose